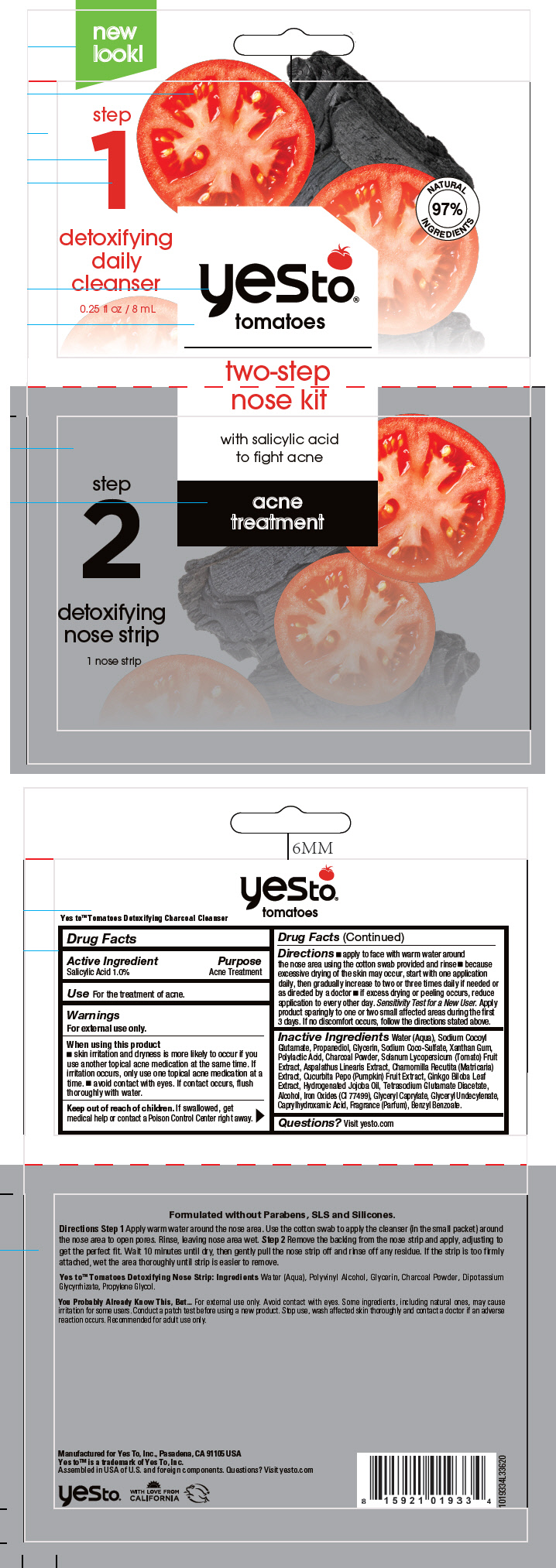 DRUG LABEL: Yes To Tomatoes Two-Step Nose
NDC: 69840-025 | Form: KIT | Route: TOPICAL
Manufacturer: Yes To Incorporated
Category: otc | Type: HUMAN OTC DRUG LABEL
Date: 20210122

ACTIVE INGREDIENTS: Salicylic Acid 10 mg/1 mL
INACTIVE INGREDIENTS: XANTHAN GUM; GLYCERIN; SODIUM COCOYL GLUTAMATE; SODIUM COCO-SULFATE; GLYCERYL MONOCAPRYLATE; GLYCERYL 1-UNDECYLENATE; PROPANEDIOL; GINKGO; CHAMOMILE; ASPALATHUS LINEARIS WHOLE; CUCURBITA PEPO WHOLE; SOLANUM LYCOPERSICUM FRUITING TOP; ALCOHOL; ACTIVATED CHARCOAL; HYDROGENATED JOJOBA OIL	; POLYLACTIDE; FERRIC OXIDE RED; WATER; TETRASODIUM GLUTAMATE DIACETATE; CAPRYLHYDROXAMIC ACID

Yes To® Tomatoes Two-Step Nose Kit

Drug Facts

Active Ingredient

Salicylic Acid 1.0%

Purpose

Acne Treatment

Use

For the treatment of acne.

Warnings

For external use only.

When using this product

- skin irritation and dryness is more likely to occur if you use another topical acne medication at the same time. If irritation occurs, only use one topical acne medication at a time.
- avoid contact with eyes. If contact occurs, flush thoroughly with water.

Keep out of reach of children. If swallowed, get medical help or contact a Poison Control Center right away.

Directions

- apply to face with warm water around the nose area using the cotton swab provided and rinse
- because excessive drying of the skin may occur, start with one application daily, then gradually increase to two or three times daily if needed or as directed by a doctor
- if excess drying or peeling occurs, reduce application to every other day.

Sensitivity Test for a New User. Apply product sparingly to one or two small affected areas during the first 3 days. If no discomfort occurs, follow the directions stated above.

Inactive Ingredients

Water (Aqua), Sodium Cocoyl Glutamate, Propanediol, Glycerin, Sodium Coco-Sulfate, Xanthan Gum, Polylactic Acid, Charcoal Powder, Solanum Lycopersicum (Tomato) Fruit Extract, Aspalathus Linearis Extract, Chamomilla Recutita (Matricaria) Extract, Cucurbita Pepo (Pumpkin) Fruit Extract, Ginkgo Biloba Leaf Extract, Hydrogenated Jojoba Oil, Tetrasodium Glutamate Diacetate, Alcohol, Iron Oxides (CI 77499), Glyceryl Caprylate, Glyceryl Undecylenate, Caprylhydroxamic Acid, Fragrance (Parfum), Benzyl Benzoate.

Questions?

Visit yesto.com

PRINCIPAL DISPLAY PANEL - Kit Packet

new
look!

step
1
detoxifying
daily
cleanser
0.25 fl oz / 8 mL

NATURAL
97%
INGREDIENTS

yesto®
tomatoes

two-step
nose kit

with salicylic acid
to fight acne

acne
treatment

step
2
detoxifying
nose strip
1 nose strip